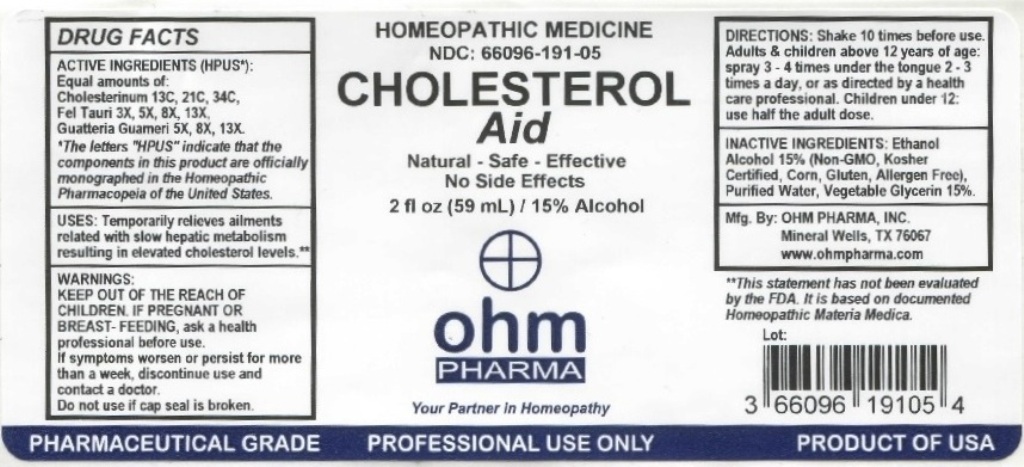 DRUG LABEL: Ohm Cholesterol Aid
NDC: 66096-191 | Form: LIQUID
Manufacturer: OHM PHARMA INC.
Category: homeopathic | Type: HUMAN OTC DRUG LABEL
Date: 20211229

ACTIVE INGREDIENTS: CHOLESTEROL 13 [hp_C]/59 mL; BOS TAURUS BILE 3 [hp_X]/59 mL; MALMEA DEPRESSA BARK 5 [hp_X]/59 mL
INACTIVE INGREDIENTS: ALCOHOL; WATER; GLYCERIN

OHM Cholesterol Aid

ACTIVE INGREDIENT

ACTIVE INGREDIENTS (HPUS*): Equal amounts of: Cholesterinum 13C, 21C, 34C, Fel Tauri 3X, 5X, 8X, 13X, Guatteria Guameri 5X, 8X, 13X.

*The letters "HPUS" indicate that the components in this product are officially monographed in the Homeopathic Pharmacopeia of the United States.

INDICATIONS AND USAGE

USES: Temporarily relieves ailments related with slow hepatic metabolism resulting in elevated cholesterol levels.**

**This statement has not been evaluated by the FDA. It is based on documented Homeopathic Materia Medica.

WARNINGS

WARNINGS: IF PREGNANT OR BREAST-FEEDING, ask a health professional before use. If symptoms worsen or persist for more than a week, discontinue use and contact a doctor.

- KEEP OUT OF REACH OF CHILDREN.

DOSAGE AND ADMINISTRATION

DIRECTIONS: Shake 10 times before use. Adults & children above 12 years of age: spray 3-4 times under the tongue every 15 minutes, extend intervals as symptoms improve or as directed by a health care professional. Children under 12: use half the adult dose.

Do not use if cap seal is broken.

INACTIVE INGREDIENT

INACTIVE INGREDIENTS: Ethanol Alcohol 15% (Non-GMO, Kosher Certified, Corn, Gluten, Allergen Free), Purified Water, Vegetable Glycerin 15%.

QUESTIONS

Mfg. By: OHM PHARMA, INC. Mineral Wells, TX 76067

www.ohmpharma.com

PACKAGE LABEL

HOMEOPATHIC MEDICINE

NDC:66096-191-05

CHOLESTEROL AID

Natural - Safe - Effective

No Side Effects

2 fl oz (59 mL) / 15% Alcohol

PRODUCT OF USA

PURPOSE

Temporarily relieves ailments related with slow hepatic metabolism resulting in elevated cholesterol levels.